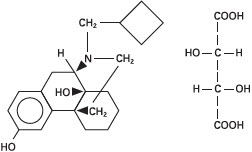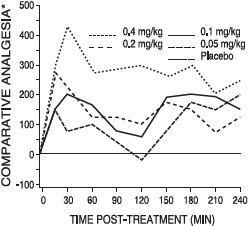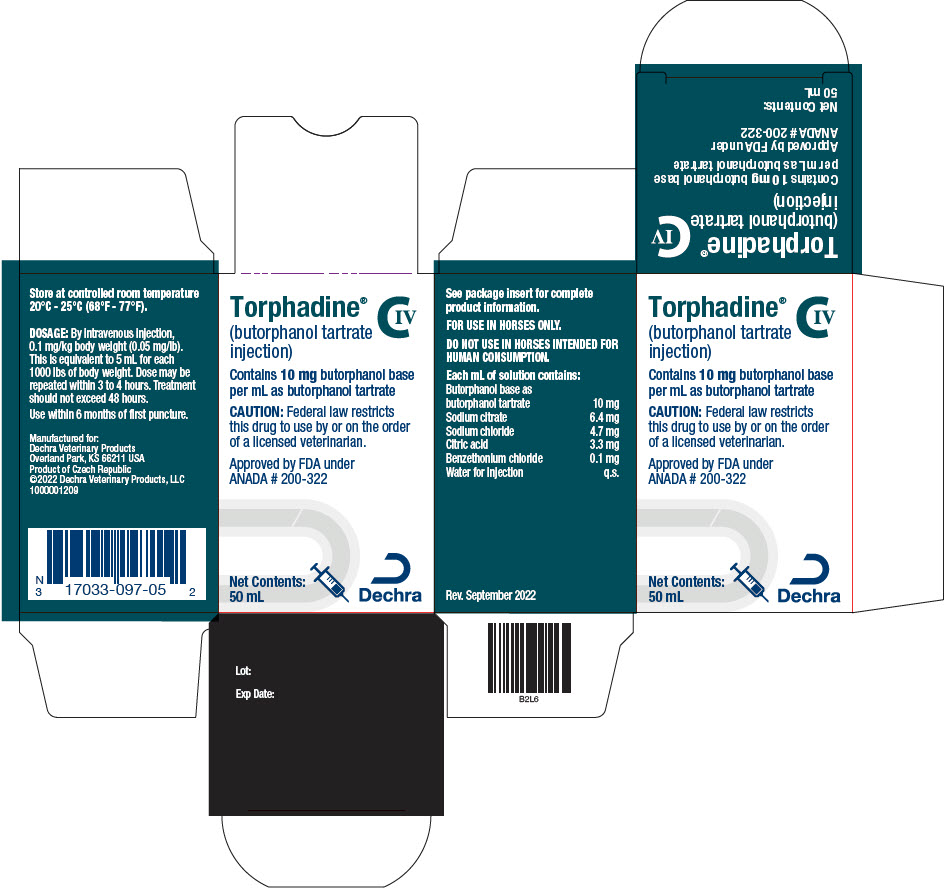 DRUG LABEL: Torphadine
NDC: 17033-097 | Form: INJECTION
Manufacturer: Dechra Veterinary Products
Category: animal | Type: PRESCRIPTION ANIMAL DRUG LABEL
Date: 20251216
DEA Schedule: CIV

ACTIVE INGREDIENTS: BUTORPHANOL TARTRATE 10 mg/1 mL
INACTIVE INGREDIENTS: CITRIC ACID MONOHYDRATE 3.3 mg/1 mL; SODIUM CITRATE 6.4 mg/1 mL; SODIUM CHLORIDE 4.7 mg/1 mL; BENZETHONIUM CHLORIDE 0.1 mg/1 mL

Torphadine® CIV
(butorphanol tartrate injection)

CAUTION

Federal law restricts this drug to use by or on the order of a licensed veterinarian.

DESCRIPTION

TORPHADINE (butorphanol tartrate injection) is a totally synthetic, centrally acting, narcotic agonist-antagonist analgesic with potent antitussive activity. It is a member of the phenanthrene series. The chemical name is Morphinan-3, 14-diol, 17-(cyclobutylmethyl)-, (-)-, (S- (R*, R*))-2, 3-dihydroxybutanedioate (1:1) (salt). It is a white, crystalline, water soluble substance having a molecular weight of 477.55; its molecular formula is C21H29NO2∙C4H6O6.

Chemical Structure |  | Each mL of TORPHADINE contains 10 mg butorphanol base (as butorphanol tartrate), 3.3 mg citric acid, 6.4 mg sodium citrate, 4.7 mg sodium chloride, and 0.1 mg benzethonium chloride, q.s. with water for injection.

CLINICAL PHARMACOLOGY

Comparative Pharmacology

In animals, butorphanol has been demonstrated to be 4 to 30 times more potent than morphine and pentazocine (Talwin®-V) respectively.^1 In humans, butorphanol has been shown to have 5-7 times the analgesic activity of morphine and 20 times that of pentazocine.^(2, 3) Butorphanol has 15 to 20 times the oral antitussive activity of codeine or dextromethorphan in dogs and guinea pigs.^4

As an antagonist, butorphanol is approximately equivalent to nalorphine and 30 times more potent than pentazocine.^1 Cardiopulmonary depressant effects are minimal after treatment with butorphanol as demonstrated in dogs^5, humans^6,7 and horses.^8 Unlike classical narcotic agonist analgesics which are associated with decreases in blood pressure, reduction in heart rate and concomitant release of histamine, butorphanol does not cause histamine release.^1 Furthermore, the cardiopulmonary effects of butorphanol are not distinctly dosage-related but rather reach a ceiling effect beyond which further dosage increases result in relatively lesser effects.

Reproduction: Studies performed in mice and rabbits revealed no evidence of impaired fertility or harm to the fetus due to butorphanol tartrate. In the female rat, parenteral administration was associated with increased nervousness and decreased care for the newborn, resulting in a decreased survival rate of the newborn. This nervousness was seen only in the rat species.

Equine Pharmacology

Following intravenous injection in horses, butorphanol is largely eliminated from the blood within 3 to 4 hours. The drug is extensively metabolized in the liver and excreted in the urine.

In ponies, butorphanol given intramuscularly at a dosage of 0.22 mg/kg, was shown to alleviate experimentally induced visceral pain for about 4 hours.^9

In horses, intravenous dosages of butorphanol ranging from 0.05 to 0.4 mg/kg were shown to be effective in alleviating visceral and superficial pain for at least 4 hours, as illustrated in the following figure:

Analgesic Effects of Butorphanol Given at Various Dosages in Horses with Abdominal Pain

*Pain threshold in butorphanol-treated colicky horses relative to placebo controls.

A definite dosage-response relationship was detected in that butorphanol dosage of 0.1 mg/kg was more effective than 0.05 mg/kg but not different from 0.2 mg/kg in alleviating deep abdominal pain.

Acute Equine Studies

Rapid intravenous administration of butorphanol at a dosage of 2 mg/kg (20 times the recommended dosage) to a previously unmedicated horse resulted in a brief episode of inability to stand, muscle fasciculation, a convulsive seizure of 6 seconds duration and recovery within three minutes.

The same dosage administered after 10 successive daily 1 mg/kg dosages of butorphanol resulted only in transient sedative effects. During the 10-day course of administration at 1 mg/kg (10 times the recommended use level) in two horses, the only detectable drug effects were transient behavioral changes typical of narcotic agonist activity.

These included muscle fasciculation about the head and neck, dysphoria, lateral nystagmus, ataxia and salivation. Repeated administration of butorphanol at 1 mg/kg (10 times the recommended dose) every four hours for 48 hours caused constipation in one of two horses.

Subacute Equine Studies

Horses were found to tolerate butorphanol given intravenously at dosages of 0.1, 0.3 and 0.5 mg/kg every 4 hours for 48 hours followed by once daily injections for a total of 21 days. The only detectable drug effects were slight transient ataxia observed occasionally in the high dosage group. No clinical, laboratory, or gross or histopathologic evidence of any butorphanol-related toxicity was encountered in the horses.

INDICATIONS

TORPHADINE (butorphanol tartrate injection) is indicated for the relief of pain associated with colic in adult horses and yearlings. Clinical studies in the horse have shown that butorphanol tartrate injection alleviates abdominal pain associated with torsion, impaction, intussusception, spasmodic and tympanic colic and postpartum pain.

WARNINGS

DO NOT USE IN HORSES INTENDED FOR HUMAN CONSUMPTION. NOT FOR HUMAN USE.

CAUTION

TORPHADINE, a potent analgesic, should be used with caution with other sedative or analgesic drugs as these are likely to produce additive effects.

There are no well-controlled studies using butorphanol in breeding horses, weanlings and foals. Therefore, the drug should not be used in these groups.

ADVERSE REACTIONS

In clinical trials in horses, the most commonly observed side effect was slight ataxia which lasted 3 to 10 minutes. Marked ataxia was reported in 1.5% of the 327 horses treated. Mild sedation was reported in 9% of the horses.

To report suspected adverse drug events, for technical assistance, or to obtain a copy of the Safety Data Sheet, contact Dechra Veterinary Products at (866) 933-2472.

For additional information about adverse drug experience reporting for animal drugs, contact FDA at 1-888-FDA-VETS or http://www.fda.gov/reportanimalae

DOSAGE

The recommended dosage in the horse is 0.1 mg of butorphanol per kilogram of body weight (0.05 mg/lb) by intravenous injection. This is equivalent to 5 mL of TORPHADINE for each 1000 lbs body weight. The dose may be repeated within 3 to 4 hours but treatment should not exceed 48 hours.

Pre-clinical model studies and clinical field trials in horses demonstrate that the analgesic effects of butorphanol tartrate injection are seen within 15 minutes following injection and persist for about 4 hours.

Use within 6 months of first puncture.

HOW SUPPLIED

10 mL and 50 mL vials TORPHADINE (butophanol tartrate injection). 10 mg base activity per mL.

STORAGE AND HANDLING

Store at controlled room temperature 20°-25°C (68°-77°F).

REFERENCES

1. Pircio, A.W. et al: "The Pharmacology of Butorphanol." Arch. Int. Pharmacodyn. Ther. 220 (2): 231-257, 1976.
2. Dobkin, A.B. et al: "Butorphanol and Pentazocine in Patients with Severe Postoperative Pain." Clin. Pharmacol. Ther. 18: 547-553, 1975.
3. Gilbert, M.S. et al: "Intramuscular Butorphanol and Meperidine in Postoperative Pain." Clin. Pharmacol. Ther. 20: 359-364, 1976.
4. Cavanagh, R.L. et al: "Antitussive Properties of Butorphanol." Arch. Int. Pharmacodyn. Ther. 220 (2): 258-268, 1976.
5. Schurig, J.E. et al: "Effect of Butorphanol and Morphine on Pulmonary Mechanics, Arterial Blood Pressure, and Venous Plasma Histamine in the Anesthetized Dog." Arch. Int. Pharmacodyn. Ther. 233: 296-304, 1978.
6. Nagashmina, H. et al: "Respiratory and Circulatory Effects of Intravenous Butorphanol and Morphine." Clin. Pharmacol. Ther. 19: 735-745, 1976.
7. Popio, K.A, et al: "Hemodynamic and Respiratory Effects of Morphine and Butorphanol." Clin. Pharmacol. Ther. 23: 281-287, 1978.
8. Robertson, J.T. and Muir, W.W.: "Cardiopulmonary Effects of Butorphanol Tartrate in Horses." Am. J. Vet. Res. 42: 41-44, 1981.
9. Kalpravidh, M. et al: "Effects of Butorphanol, Flunixin, Levorphanol, Morphine, Pentazocine and Xylazine in Ponies." Am. J. Vet. Res. 45: 217-223, 1984.

Approved by FDA under ANADA # 200-322

Manufactured for:
Dechra Veterinary Products
7015 College Boulevard, Suite 525
Overland Park, KS 66211 USA

©2022 Dechra Veterinary Products, LLC
Rev. September 2022

1000001776

Dechra

PRINCIPAL DISPLAY PANEL - 50 mL Vial Carton

Torphadine®
(butorphanol tartrate
injection)
CIV

Contains 10 mg butorphanol base
per mL as butorphanol tartrate

CAUTION: Federal law restricts
this drug to use by or on the order
of a licensed veterinarian.

Approved by FDA under
ANADA # 200-322

Net Contents:
50 mL

Dechra